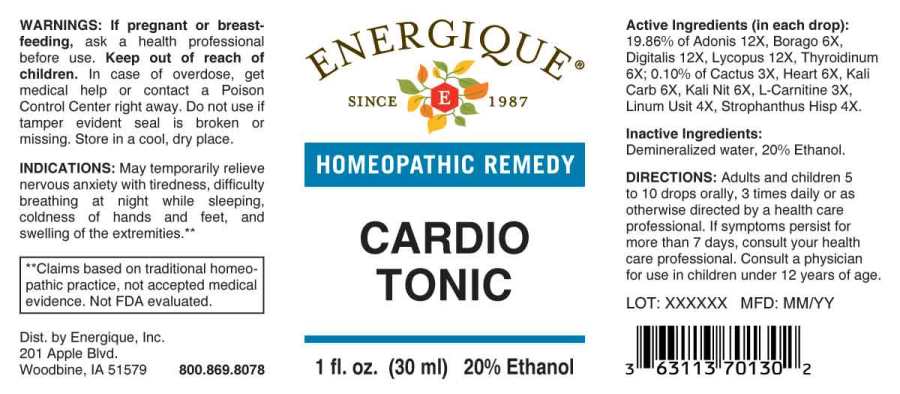 DRUG LABEL: Cardio Tonic
NDC: 44911-0409 | Form: LIQUID
Manufacturer: Energique, Inc.
Category: homeopathic | Type: HUMAN OTC DRUG LABEL
Date: 20241024

ACTIVE INGREDIENTS: SELENICEREUS GRANDIFLORUS STEM 3 [hp_X]/1 mL; LEVOCARNITINE 3 [hp_X]/1 mL; FLAX SEED 4 [hp_X]/1 mL; STROPHANTHUS HISPIDUS SEED 4 [hp_X]/1 mL; BORAGE 6 [hp_X]/1 mL; PORK HEART 6 [hp_X]/1 mL; POTASSIUM CARBONATE 6 [hp_X]/1 mL; POTASSIUM NITRATE 6 [hp_X]/1 mL; THYROID 6 [hp_X]/1 mL; ADONIS VERNALIS WHOLE 12 [hp_X]/1 mL; DIGITALIS 12 [hp_X]/1 mL; LYCOPUS VIRGINICUS WHOLE 12 [hp_X]/1 mL
INACTIVE INGREDIENTS: WATER; ALCOHOL

DRUG FACTS:

ACTIVE INGREDIENTS:

(in each drop): 19.86% of Adonis Vernalis 12X, Borago Officinalis 6X, Digitalis Purpurea 12X, Lycopus Virginicus 12X, Thyroidinum (Suis) 6X; 0.10% of Cactus Grandiflorus 3X, Heart (Suis) 6X, Kali Carbonicum 6X, Kali Nitricum 6X, L-Carnitine 3X, Linum Usitatissimum 4X, Strophanthus Hispidus 4X.

INDICATIONS:

May temporarily relieve nervous anxiety with tiredness, difficulty breathing at night while sleeping, coldness of hands and feet, and swelling of the extremities.**

**Claims based on traditional homeopathic practice, not accepted medical evidence. Not FDA evaluated.

WARNINGS:

If pregnant or breastfeeding, ask a health professional before use.

Keep out of reach of children. In case of overdose, get medical help or contact a Poison Control Center right away.

Do not use if tamper evident seal is broken or missing.

Store in a cool, dry place.

Keep out of reach of children. In case of overdose, get medical help or contact a Poison Control Center right away.

DIRECTIONS:

Adults and children 5 to 10 drops orally, 3 times daily or as otherwise directed by a health care professional. If symptoms persist for more than 7 days, consult your health care professional. Consult a physician for use in children under 12 years of age.

INDICATIONS:

May temporarily relieve nervous anxiety with tiredness, difficulty breathing at night while sleeping, coldness of hands and feet, and swelling of the extremities.**

**Claims based on traditional homeopathic practice, not accepted medical evidence. Not FDA evaluated.

INACTIVE INGREDIENTS:

Demineralized water, 20% Ethanol.

QUESTIONS:

Dist. by Energique, Inc.
201 Apple Blvd.
Woodbine, IA 51579 800.869.8078

PACKAGE LABEL DISPLAY:

ENERGIQUE
SINCE 1987
HOMEOPATHIC REMEDY
CARDIO
TONIC
1 fl. oz. (30 ml)